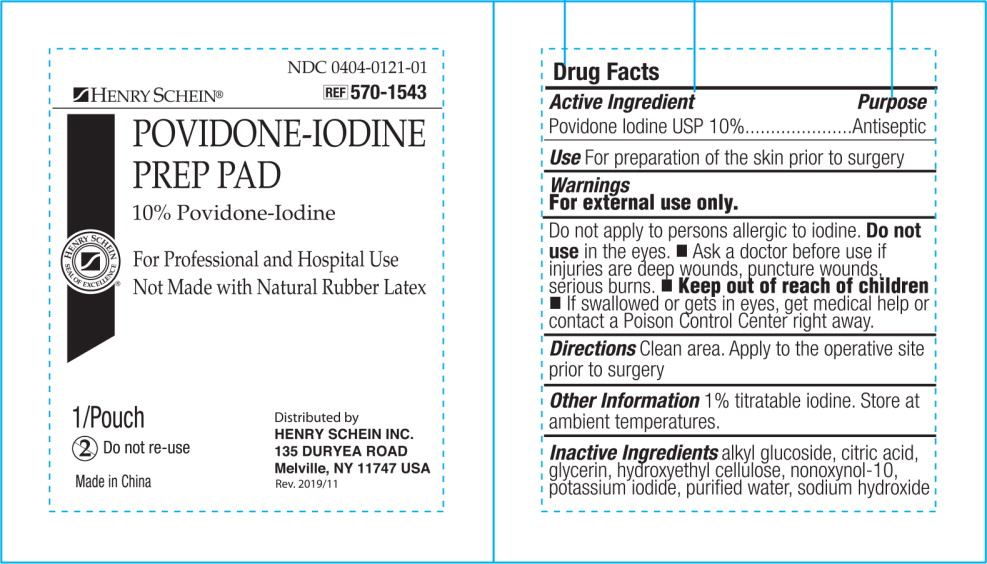 DRUG LABEL: Henry Schein Povidone-Iodine Prep Pad
NDC: 0404-0121 | Form: SWAB
Manufacturer: Henry Schein, Inc.
Category: otc | Type: HUMAN OTC DRUG LABEL
Date: 20231013

ACTIVE INGREDIENTS: POVIDONE-IODINE 1 g/100 mL
INACTIVE INGREDIENTS: GLYCERIN; HYDROXYETHYL CELLULOSE (2000 MPA.S AT 1%); NONOXYNOL-10; ANHYDROUS CITRIC ACID; SODIUM HYDROXIDE; WATER; POTASSIUM IODIDE

Drug Facts

Active ingredient

Povidone Iodine USP 10%

Purpose

Antiseptic

Use

For preparation of the skin prior to surgery

Warnings

For external use only.

Do not apply to persons allergic to iodine.

Do not use in the eyes.

- Ask a doctor before use if injuries are deep wounds, puncture wounds, serious burns.

- Keep out of reach of children
- If swallowed or gets in eyes, get medical help or contact a Poison Control Center right away.

Directions

Clean area. Apply to the operative site prior to surgery

Other information

- 1 % titratable iodine. Store at ambient temperatures

Inactive ingredients

alkyl glucoside, citric acid, glycerin, hydroxyethyl cellulose, nonoxynol-10, potassium iodide, purified water, sodium hydroxide

Principal Display Panel - 0.5 mL Item Label

NDC 0404-0121-01

HENRY SCHEIN®

REF 570-1543

POVIDONE-IODINE
PREP PAD

10% Povidone-Iodine

For Professional and Hospital Use

Not Made with Natural Rubber Latex

HENRY SCHEIN
SEAL OF EXCELLENCE®

1/Pouch